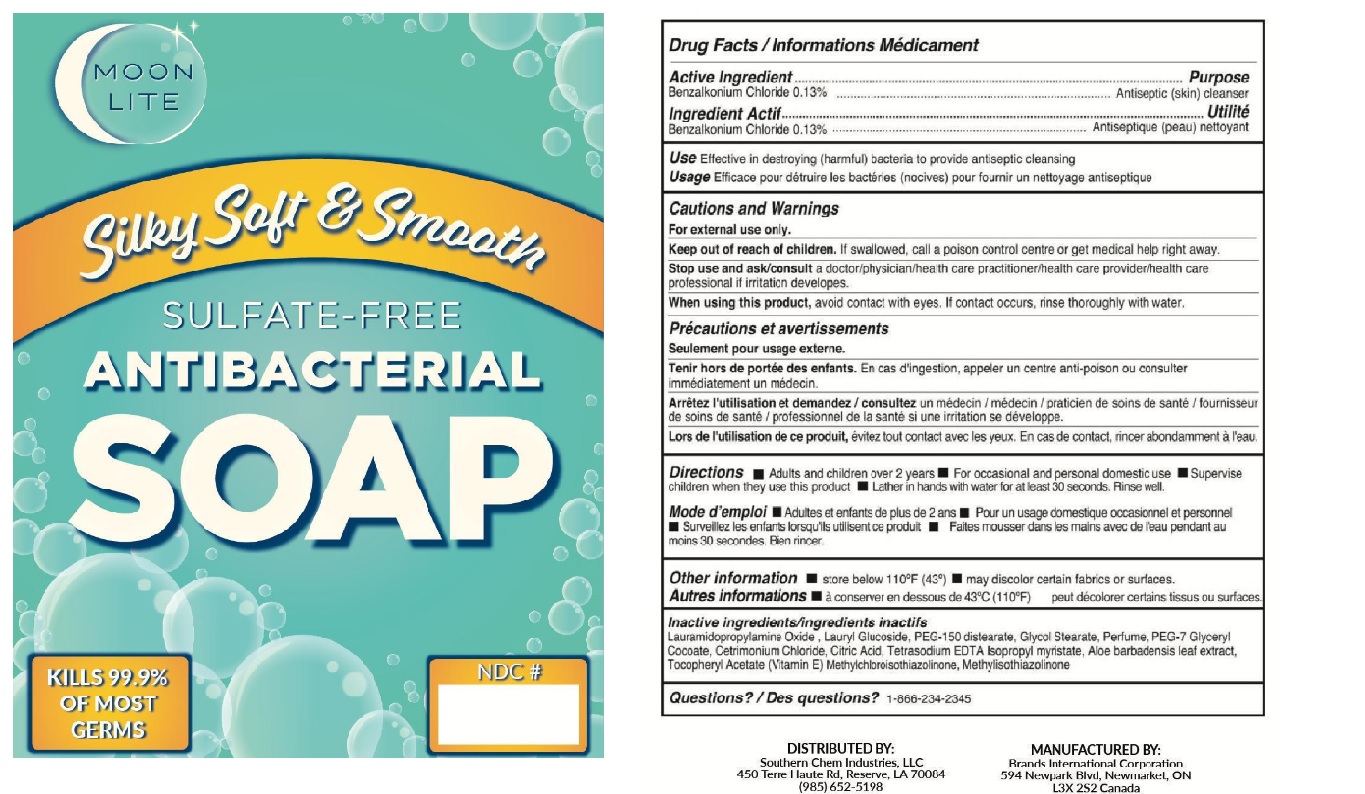 DRUG LABEL: Moonlite Antibacterial
NDC: 50157-511 | Form: LIQUID
Manufacturer: Brands International Corporation
Category: otc | Type: HUMAN OTC DRUG LABEL
Date: 20200923

ACTIVE INGREDIENTS: BENZALKONIUM CHLORIDE 1.3 mg/1 mL
INACTIVE INGREDIENTS: LAURAMIDOPROPYLAMINE OXIDE; LAURYL GLUCOSIDE; PEG-150 DISTEARATE; GLYCOL STEARATE; WATER; PEG-7 GLYCERYL COCOATE; CITRIC ACID MONOHYDRATE; CETRIMONIUM CHLORIDE; EDETATE SODIUM; ISOPROPYL MYRISTATE; ALOE VERA LEAF; METHYLCHLOROISOTHIAZOLINONE; METHYLISOTHIAZOLINONE; .ALPHA.-TOCOPHEROL ACETATE

Moon Lite Antibacterial Soap: Sulfate-Free

ACTIVE INGREDIENT

Benzalkonium Chloride - 0.13%

Purpose - Antiseptique(skin)cleanser

INDICATIONS AND USAGE

Uses Effective in destorying(harmful) bacteria to provide antiseptic cleansing.

WARNINGS

Warning For external use only

Stop use and ask a doctor if irritation or redness develops

When using the product

- avoid contact wiith eyes. If contact occurs rinse eye thoroughly with water

Keep out of reach of children

If swallowed, get medical help or contact a Poison Control Center right away

DOSAGE AND ADMINISTRATION

Direction

- Adults and children over 2 year
- For occasional and personal domestic use
- Supervise children when use this product
- Lather in hands with water for at least 30 seconds
- Rinse well

OTHER SAFETY INFORMATION

- Store below 110F(43)
- May discolor certain fabrics or surfaces.

INACTIVE INGREDIENT

Water,Lauramidopropylamine Oxide (Triaminox LO), Lauryl Glucoside, Citric Acid, PEG-150 distearate, Glycol Stearate, PEG-7 Glyceryl Cocoate,Cetrimonium Chloride, Tetrasodium EDTA,Isopropyl myristate, Aloe Leaf, Tocopheryl Acetate, Methylchloroisothiazolinone, Methylisothiazolinone,